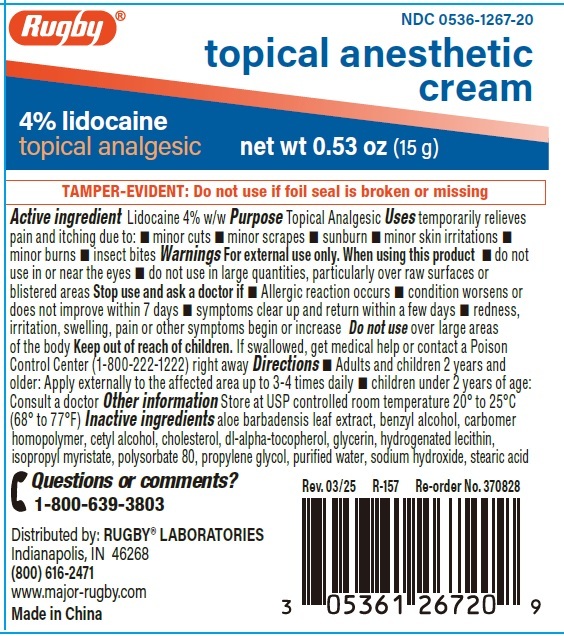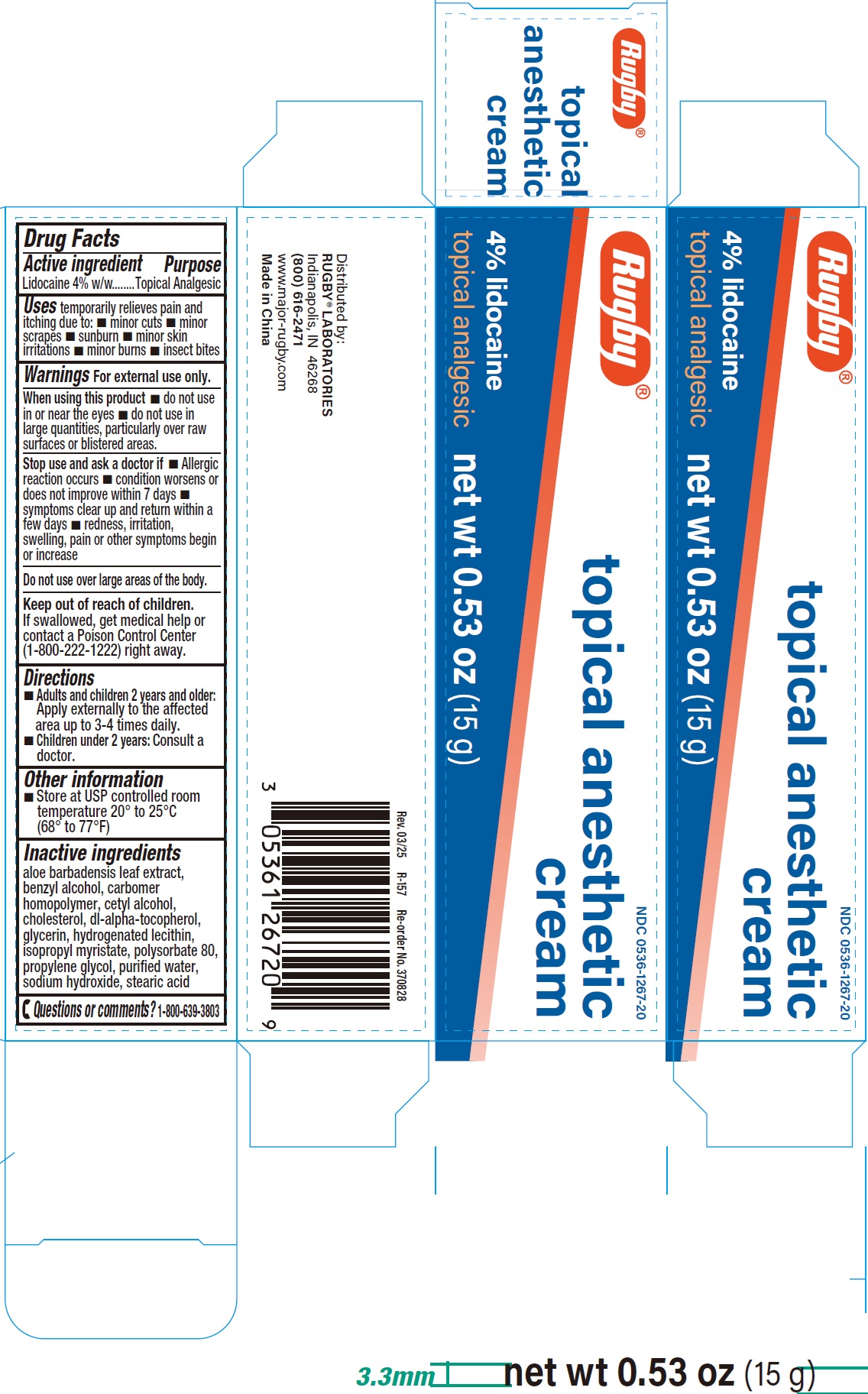 DRUG LABEL: 4 Lidocaine Topical Anesthetic
NDC: 0536-1267 | Form: CREAM
Manufacturer: RUGBY LABORATORIES
Category: otc | Type: HUMAN OTC DRUG LABEL
Date: 20250627

ACTIVE INGREDIENTS: LIDOCAINE 40 mg/1 g
INACTIVE INGREDIENTS: ALOE VERA LEAF; BENZYL ALCOHOL; CARBOMER HOMOPOLYMER, UNSPECIFIED TYPE; CETYL ALCOHOL; CHOLESTEROL; .ALPHA.-TOCOPHEROL, DL-; GLYCERIN; HYDROGENATED SOYBEAN LECITHIN; ISOPROPYL MYRISTATE; POLYSORBATE 80; PROPYLENE GLYCOL; WATER; SODIUM HYDROXIDE; STEARIC ACID

4% Lidocaine Topical Anesthetic Cream

Active ingredient

Lidocaine 4% W/W

Purpose

Topical Analgesic

Uses

temporarily relieves pain and itching due to:

- minor cuts
- minor scrapes
- sunburn
- minor skin irritations
- minor burns
- insect bites

Warnings

For external use only.

When using this product

- do not use in or near the eyes
- do not use in large quantities, particularly over raw surfaces or blistered areas.

Stop use and ask a doctor if

- Allergic reaction occurs
- condition worsens or does not improve within 7 days
- symptoms clear up and return within a few days
- redness, irritation, swelling, pain or other symptoms begin or increase

Do not use

over large areas of the body.

Keep out of reach of children.

If swallowed, get medical help or contact a Poison Control Center (1-800-222-1222) right away.

Directions

- Adults and children 2 years and older: Apply externally to the affected area up to 3-4 times daily.
- Children under 2 years:Consult a doctor.

Other information

- Store at USP controlled room temperature 20° to 25°C (68° to 77°F)

Inactive ingredient

aloe barbadensis leaf extract, benzyl alcohol, carbomer homopolymer, cetyl alcohol, cholesterol, di-alpha tocopherol, glycerin, hydrogenated lecithin, isopropyl myristate, polysorbate 80, propylene glycol, purified water, stearic acid

Questions or comments?

1-800-639-3803